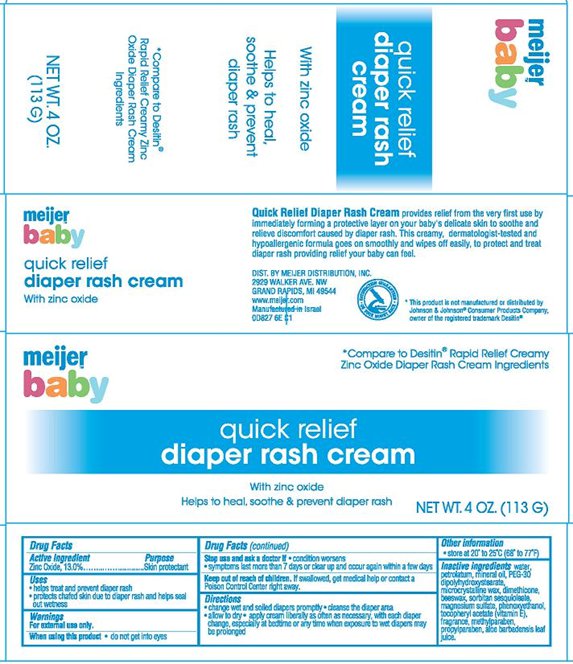 DRUG LABEL: Meijer Baby Quick Relief Diaper Rash
NDC: 41250-827 | Form: CREAM
Manufacturer: Meijer Distribution Inc.
Category: otc | Type: HUMAN OTC DRUG LABEL
Date: 20140114

ACTIVE INGREDIENTS: ZINC OXIDE 13 g/100 g
INACTIVE INGREDIENTS: WATER; PETROLATUM; MINERAL OIL; PEG-30 DIPOLYHYDROXYSTEARATE; MICROCRYSTALLINE WAX; DIMETHICONE; WHITE WAX; SORBITAN SESQUIOLEATE; MAGNESIUM SULFATE; PHENOXYETHANOL; .ALPHA.-TOCOPHEROL ACETATE; METHYLPARABEN; PROPYLPARABEN; ALOE VERA LEAF

meijer baby quick relief diaper rash cream

Active ingredient

Zinc Oxide........13.0%

Purpose

Skin Protectant

Uses

- helps treat and prevent diaper rash
- protects chafed skin due to diaper rash and helps seal out wetness

Warnings

For external use only.

When using this product

- do not get into eyes

Stop use and ask a doctor if

- condition worsens
- symptoms last more than 7 days or clear up and occur again within a few days

Keep Out of Reach of Children.

If swallowed, get medical help or contact a Poison Control Center right away.

Directions

- change wet and soiled diapers promptly
- cleanse the diaper area
- allow to dry
- apply cream liberally as often as necessary, with each diaper change, especially at bedtime or any time when exposure to wet diapers may be prolonged

Other Information

- store at 20º to 25ºC (68º to 77ºF)

Inactive ingredients

water, petrolatum, mineral oil, PEG-30 dipolyhydroxysterate, microcrystalline wax, dimethicone, beeswax, sorbitan sesquioleate, magnesium sulfate, phenoxyethanol, tocopheryl acetate (vitamin E), fragrance, methylparaben, propylparaben, aloe barbadensis leaf juice.

Package/Label Principal Display Panel

meijer baby quick relief diaper rash cream

With zinc oxide

Helps to heal, soothe & prevent diaper rash

*Compare to Desitin®

Rapid Relief Creamy Zinc Oxide Diaper Rash Cream ingredients

NET WT. 4 OZ. (113 G)

Quick Relief Diaper Rash Cream provides relief from the very first use by immediately forming a protective layer on your baby's delicate skin to soothe and relieve discomfort caused by diaper rash. This creamy, dermatologist-tested and hypoallergenic formula goes on smoothly and wipes off easily, to protect and treat diaper rash providing relief you baby can feel.

DIST. BY MEIJER DISTRIBUTION, INC.
2929 WALKER AVE. NW
GRAND RAPIDS, MI 49544
www.meijer.com

Manufactured in Israel
0D827 6E C1

*This product is not manufactured or distributed by Johnson & Johnson® Consumer Products Company, owner of the registered trademark Desitin®

Carton Label